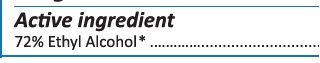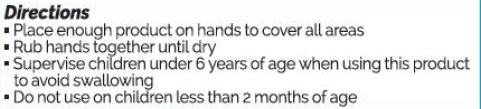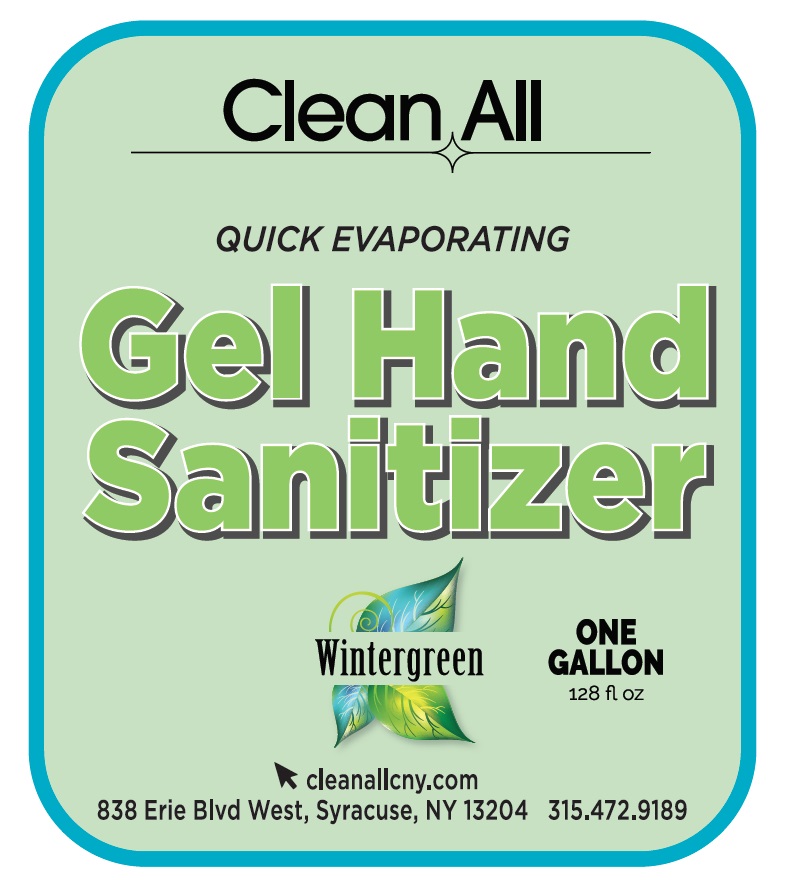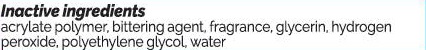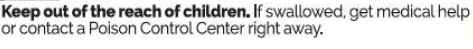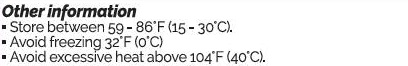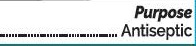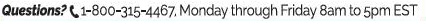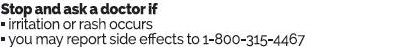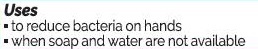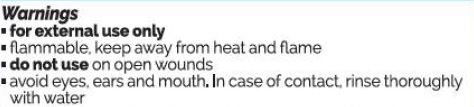 DRUG LABEL: Clean All Gel Hand Sanitizer
NDC: 75660-023 | Form: GEL
Manufacturer: Solvents and Petroleum Service, Inc
Category: otc | Type: HUMAN OTC DRUG LABEL
Date: 20201201

ACTIVE INGREDIENTS: ALCOHOL 72 mL/100 mL
INACTIVE INGREDIENTS: FRAGRANCE MINT ORC2000774 0.01 mL/100 mL; POLYETHYLENE GLYCOL, UNSPECIFIED 1.5 mL/100 mL; DENATONIUM BENZOATE 0.01 mL/100 mL; ACRYLATES/VINYL ISODECANOATE CROSSPOLYMER (10000 MPA.S NEUTRALIZED AT 0.5%) 0.5 mL/100 mL; GLYCERIN 1.35 mL/100 mL; HYDROGEN PEROXIDE 0.18 mL/100 mL; WATER 24.45 mL/100 mL

Wintergreen Gel 72% Hand Saniizer

Active Ingredient

Active ingredient 72% Ethyl Alcohol

Purpose

Antiseptic, Hand Sanitizer

Use

help reduce bacteria on hands.

when soap and water are not available.

Warnings

For external use only.

Flammable. Keep away from heat or flame

Do not use on open wounds

avoid eyes, ears and mouth. In case of contact rinse thoroughly with water

Stop and ask doctor

irritation or rash occurs

you may report side effects to 1-800-315-4467

Keep out of reach of children. If swallowed, get medical help or contact a Poison Control Center right away.

Directions

- Place enough product on hands to cover all surfaces. Rub hands together until dry.
- Supervise children under 6 years of age when using this product to avoid swallowing.

Other information

- Store between 15-30C (59-86F)
- Avoid freezing and excessive heat above 40C (104F)

Inactive ingredients

acrylate polyymer, bittering agent, fragrance, glycerin, hydrogen peroxide, polyethylene glycol, water

Questions

+

Questions? 1-800-315-4467, Monday through Friday 8am-5pm EST